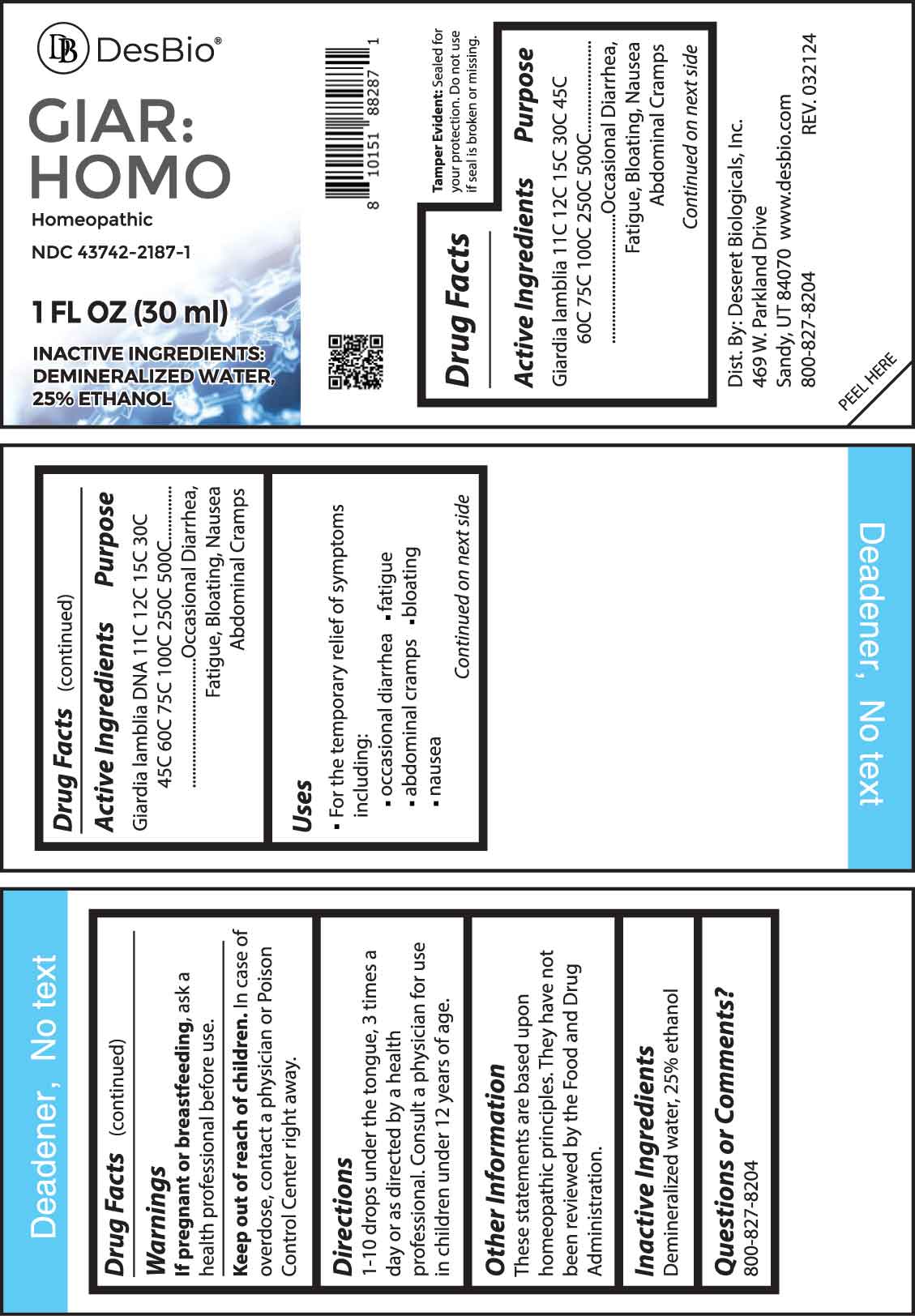 DRUG LABEL: GIAR HOMO
NDC: 43742-2187 | Form: LIQUID
Manufacturer: Deseret Biologicals, Inc
Category: homeopathic | Type: HUMAN OTC DRUG LABEL
Date: 20240814

ACTIVE INGREDIENTS: GIARDIA LAMBLIA 11 [hp_C]/1 mL; GIARDIA LAMBLIA DNA 11 [hp_C]/1 mL
INACTIVE INGREDIENTS: WATER; ALCOHOL

DRUG FACTS:

ACTIVE INGREDIENT:

Giardia Lamblia 11C, 12C, 15C, 30C, 45C, 60C, 75C, 100C, 250C, 500C, Giardia Lamblia DNA 11C, 12C, 15C, 30C, 45C, 60C, 75C, 100C, 250C, 500C.

PURPOSE:

Giardia Lamblia - Occasional Diarrhea, Fatigue, Bloating, Nausea, Abdominal Cramps, Giardia Lamblia DNA - Occasional Diarrhea, Fatigue, Bloating, Nausea, Abdominal Cramps

USES:

• For the temporary relief of symptoms including:

• occasional diarrhea • fatigue • abdominal cramps • bloating • nausea

These statements are based upon homeopathic principles. They have not been reviewed by the Food and Drug Administration.

WARNINGS:

If pregnant or breast-feeding, ask a health professional before use.

Keep out of reach of children. In case of overdose, contact a physician or Poison Control Center right away.

Tamper Evident: Sealed for your protection. Do not use if seal is broken or missing.

KEEP OUT OF REACH OF CHILDREN:

In case of overdose, contact a physician or Poison Control Center right away.

DIRECTIONS:

1-10 drops under the tongue, 3 times a day or as directed by a health professional. Consult a physician for use in children under 12 years of age.

INACTIVE INGREDIENTS:

Demineralized water, 25% ethanol

QUESTIONS:

Dist. By: Deseret Biologicals, Inc.

469 Parkland Drive

Sandy, UT 84070

www.desbio.com

800-827-8204

PACKAGE LABEL DISPLAY:

DesBio

GIAR:HOMO

Homeopathic

NDC 43742-2187-1

1 FL OZ (30 ml)